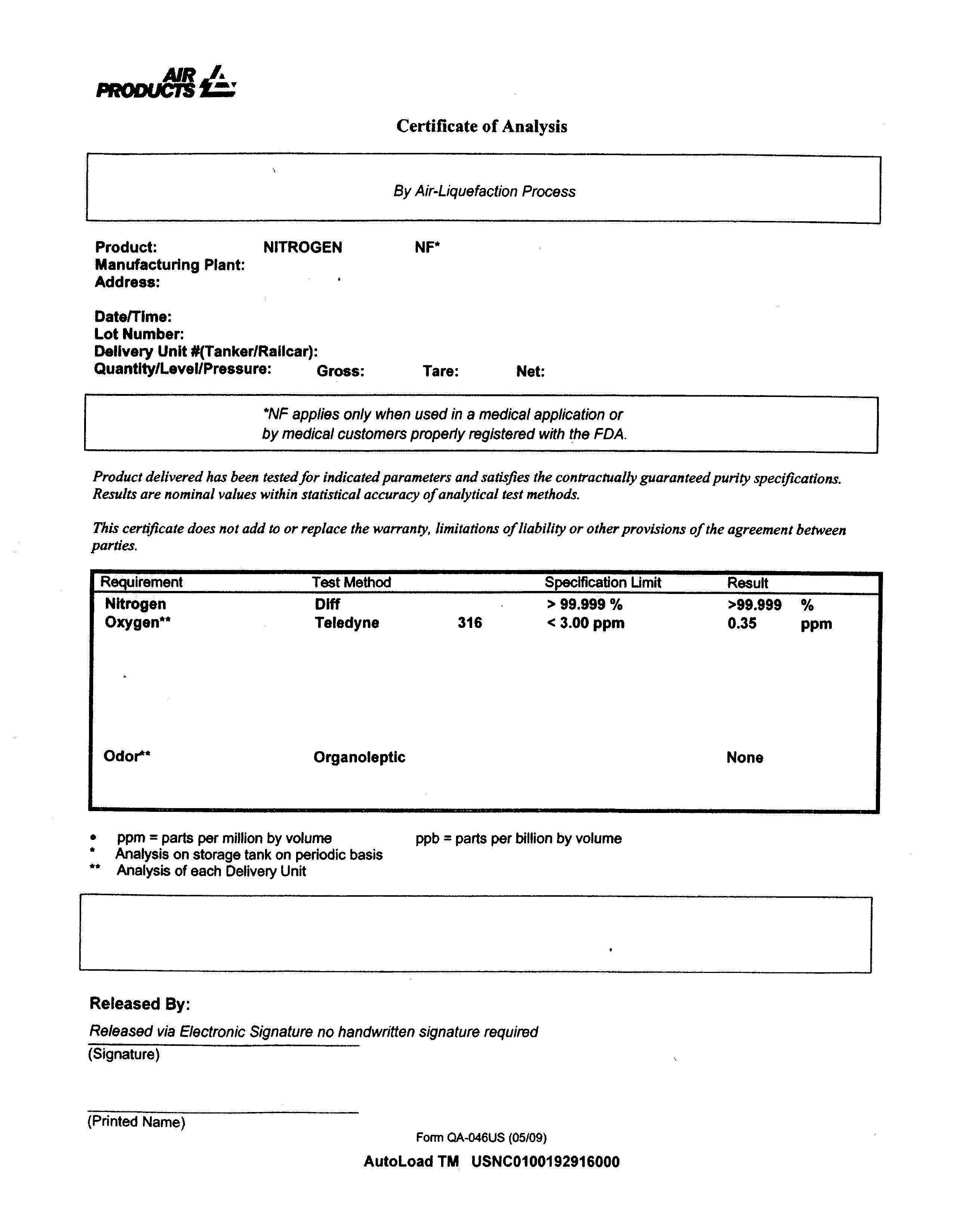 DRUG LABEL: Nitrogen
NDC: 10018-9502 | Form: GAS
Manufacturer: Air Products and Chemicals, Inc.
Category: prescription | Type: HUMAN PRESCRIPTION DRUG LABEL
Date: 20181214

ACTIVE INGREDIENTS: Nitrogen  990 mL/1 L

PACKAGE LABEL

Nitrogen